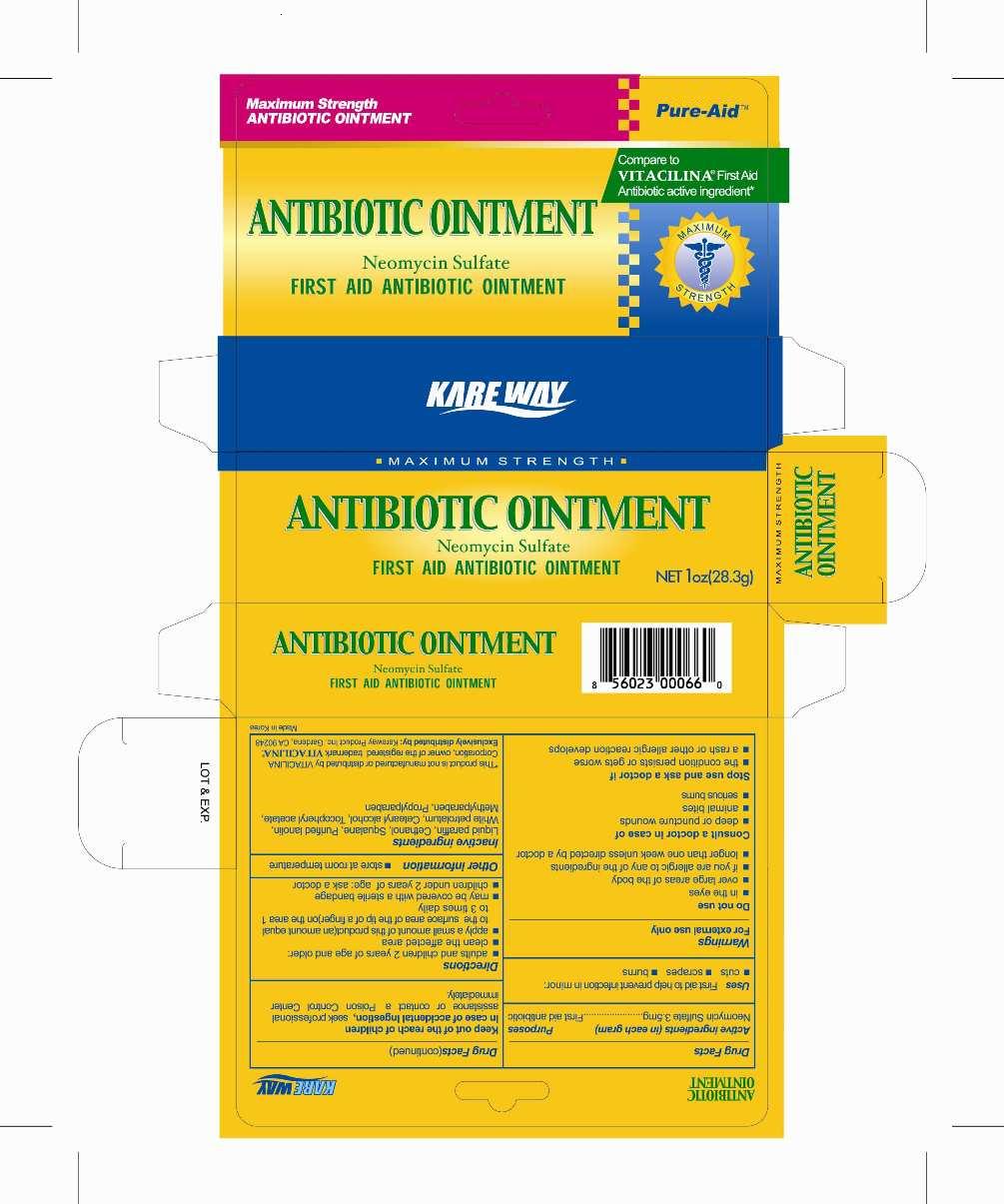 DRUG LABEL: Antibiotic
NDC: 67510-0066 | Form: OINTMENT
Manufacturer: Kareway Product, Inc.
Category: otc | Type: HUMAN OTC DRUG LABEL
Date: 20180322

ACTIVE INGREDIENTS: NEOMYCIN SULFATE 3.5 mg/1 g
INACTIVE INGREDIENTS: PARAFFIN; SQUALANE; LANOLIN; PETROLATUM; CETOSTEARYL ALCOHOL; .ALPHA.-TOCOPHEROL ACETATE, D-; METHYLPARABEN; PROPYLPARABEN

Drug Facts

Active ingredient (in each gram)

Neomycin Sulfate 3.5mg

Purposes

First aid antibiotic

Uses

First aid to help prevent infection in minor

- cuts
- scrapes
- burns

Warnings

For external use only

Do not use

- in the eyes
- over large areas of the body
- if you are allergic to any of the ingredients
- longer than one week unless directed by a doctor

Consult a doctor in case of

- deep or puncture wounds
- animal bites
- serious burns

Stop use and ask a doctor if

- the condition persists or gets worse
- a rash or other allergic reaction develops

Keep out of reach of children

In case of accidental ingestion, seek professional assistance or contact a Poison Control Center immediately.

Directions

- adults and children 2 years of age and older:
-
  - clean the affected area
  - apply a small amount of this product (an amount equal to the surface area of the tip of a finer) on the area 1 to 3 times daily
  - may be covered with a sterile bandage
- children under 2 years of age: ask a doctor

Other information

- store at room temperature

Inactive ingredients

Liquid paraffin, Cethanol, Squalane, Purified lanolin, White petrolatum, Cetearyl alcohol, Tocopheryl acetate,

Methylparaben, Propylparaben

Package label

Antibiotic Ointment